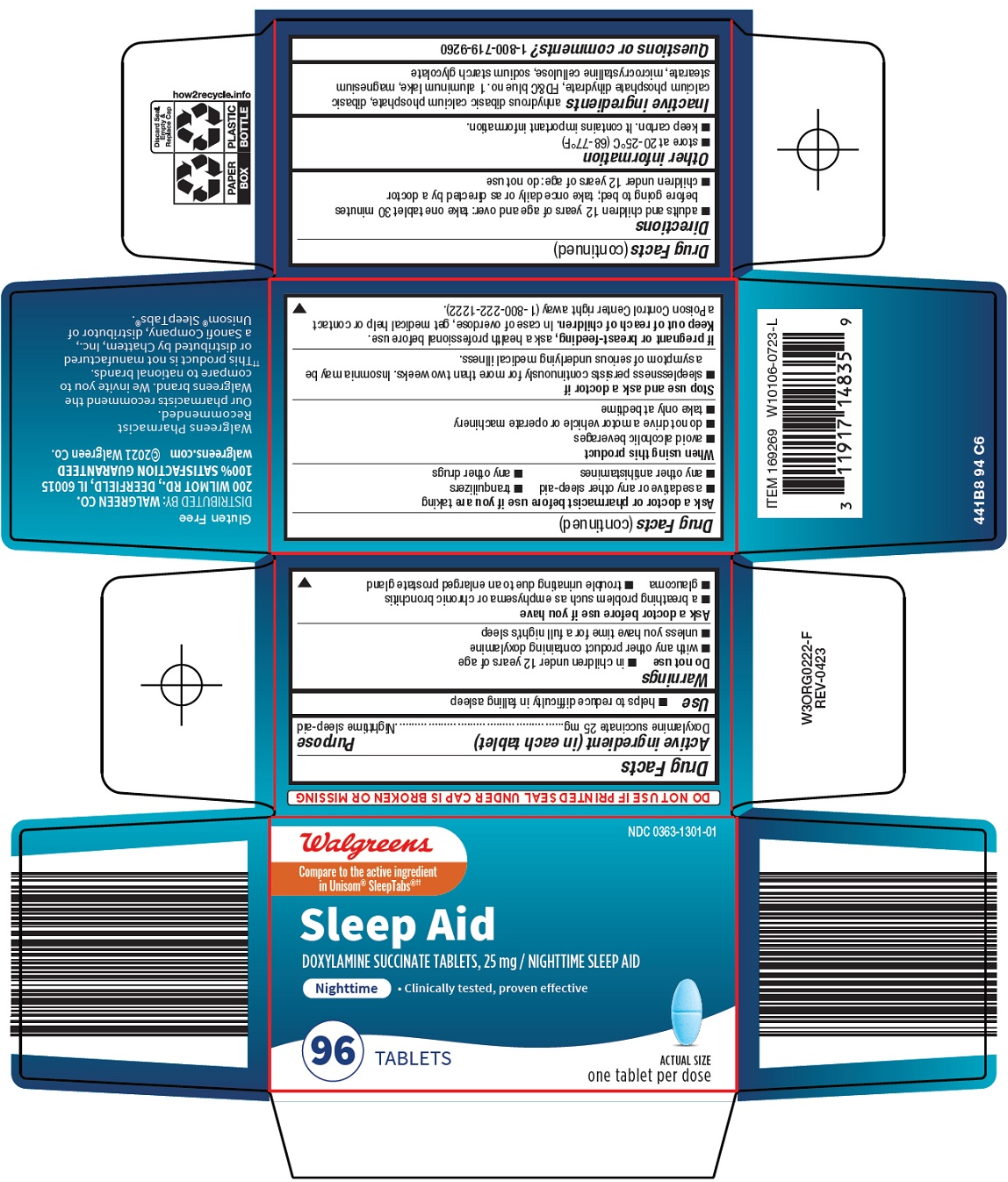 DRUG LABEL: sleep aid
NDC: 0363-1301 | Form: TABLET
Manufacturer: Walgreen Company
Category: otc | Type: HUMAN OTC DRUG LABEL
Date: 20260226

ACTIVE INGREDIENTS: DOXYLAMINE SUCCINATE 25 mg/1 1
INACTIVE INGREDIENTS: ANHYDROUS DIBASIC CALCIUM PHOSPHATE; DIBASIC CALCIUM PHOSPHATE DIHYDRATE; FD&C BLUE NO. 1 ALUMINUM LAKE; MAGNESIUM STEARATE; MICROCRYSTALLINE CELLULOSE; SODIUM STARCH GLYCOLATE TYPE A

Walgreen Co. Sleep Aid Drug Facts

Active ingredient (in each tablet)

Doxylamine succinate 25 mg

Purpose

Nighttime sleep-aid

Use

- helps to reduce difficulty in falling asleep

Warnings

Do not use

- in children under 12 years of age
- with any other product containing doxylamine
- unless you have time for a full night’s sleep

Ask a doctor before use if you have

- a breathing problem such as emphysema or chronic bronchitis
- glaucoma
- trouble urinating due to an enlarged prostate gland

Ask a doctor or pharmacist before use if you are

taking

- a sedative or any other sleep-aid
- tranquilizers
- any other antihistamines
- any other drugs

When using this product

- avoid alcoholic beverages
- do not drive a motor vehicle or operate machinery
- take only at bedtime

Stop use and ask a doctor if

- sleeplessness persists continuously for more than two weeks. Insomnia may be a symptom of serious underlying medical illness.

If pregnant or breast-feeding,

ask a health professional before use.

Keep out of reach of children.

In case of overdose, get medical help or contact a Poison Control Center right away (1-800-222-1222).

Directions

- adults and children 12 years of age and over: take one tablet 30 minutes before going to bed; take once daily or as directed by a doctor
- children under 12 years of age: do not use

Other information

- store at 20-25°C (68-77°F)
- keep carton. It contains important information.

Inactive ingredients

anhydrous dibasic calcium phosphate, dibasic calcium phosphate dihydrate, FD&C blue no. 1 aluminum lake, magnesium stearate, microcrystalline cellulose, sodium starch glycolate

Questions or comments?

1-800-719-9260

Principal Display Panel

Walgreens

Compare to the active ingredient in Unisom® SleepTabs®

Sleep Aid

DOXYLAMINE SUCCINATE TABLETS, 25 mg / NIGHTTIME SLEEP AID

Nighttime

• Clinically tested, proven effective

96 TABLETS

ACTUAL SIZE

one tablet per dose